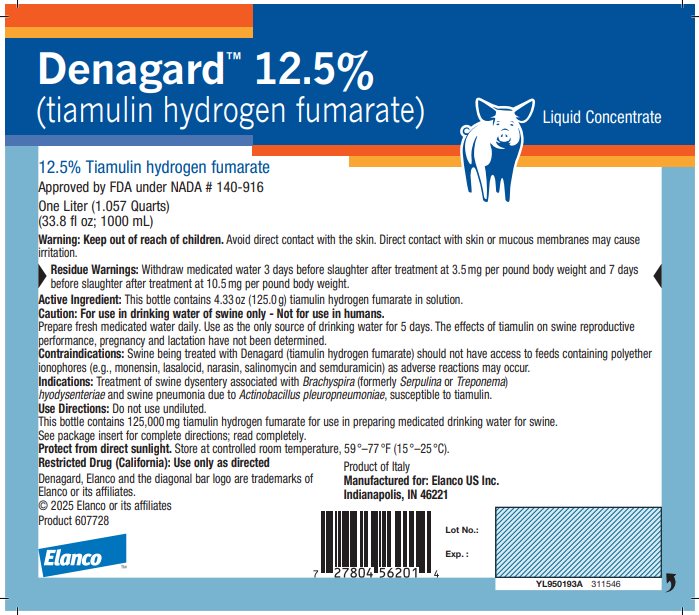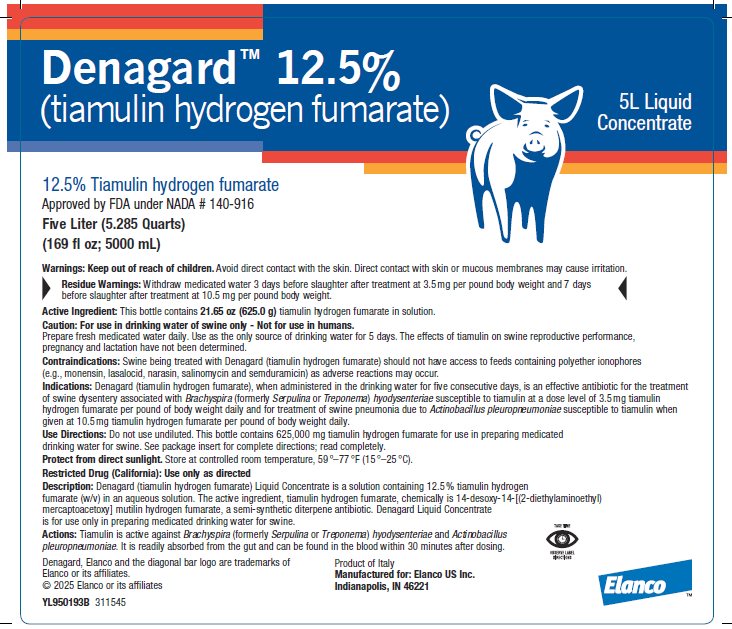 DRUG LABEL: Denagard
NDC: 58198-7425 | Form: CONCENTRATE
Manufacturer: Elanco US Inc.
Category: animal | Type: OTC ANIMAL DRUG LABEL
Date: 20250807

ACTIVE INGREDIENTS: tiamulin fumarate 0.125 g/1 mL

Denagard™ 12.5%
(tiamulin hydrogen fumarate)

Liquid Concentrate

12.5% Tiamulin hydrogen fumarate

Approved by FDA under NADA # 140-916
One Liter (1.057 Quarts)

(33.8 fl oz; 1000 mL)
Five Liter (5.285 Quarts)

(169 fl oz; 5000 mL)

Warnings:

Keep out of reach of children. Avoid contact with the skin. Direct contact with skin or mucous membranes may cause irritation.

Residue Warnings:

Withdraw medicated water 3 days before slaughter after treatment at 3.5 mg per pound body weight and 7 days before slaughter after treatment at 10.5 mg per pound body weight.

Active Ingredient:

One Liter Liquid Concentrate

This bottle contains 4.33 oz (125.0 g) tiamulin hydrogen fumarate in solution.

Five Liter Liquid Concentrate

This bottle contains 21.65 oz (625.0 g) tiamulin hydrogen fumarate in solution.

Caution:

For use in drinking water of swine only - Not for use in humans.

Prepare fresh medicated water daily. Use as the only source of drinking water for 5 days. The effects of tiamulin on swine reproductive performance, pregnancy and lactation have not been determined.

Contraindications:

Swine being treated with Denagard (tiamulin hydrogen fumarate) should not have access to feeds containing polyether ionophores (e.g., monensin, lasalocid, narasin, salinomycin and semduramicin) as adverse reactions may occur.

Indications and Usage:

One Liter Liquid Concentrate

Indications: Treatment of swine dysentery associated with Brachyspira (formerly Serpulina or Treponema) hyodysenteriae and swine pneumonia due to Actinobacillus pleuropneumoniae, susceptible to tiamulin.

Use Directions: Do not use undiluted.

This bottle contains 125,000 mg tiamulin hydrogen fumarate for use in preparing medicated drinking water for swine.

See package insert for complete directions; read completely.
Five Liter Liquid Concentrate

Indications: Denagard (tiamulin hydrogen fumarate), when administered in the drinking water for five consecutive days, is an effective antibiotic for the treatment of swine dysentery associated with Brachyspira (formerly Serpulina or Treponema) hyodysenteriae susceptible to tiamulin at a dose level of 3.5 mg tiamulin hydrogen fumarate per pound of body weight daily and for treatment of swine pneumonia due to Actinobacillus pleuropneumoniae susceptible to tiamulin when given at 10.5 mg tiamulin hydrogen fumarate per pound of body weight daily.

Use Directions: Do not use undiluted. This bottle contains 625,000 mg tiamulin hydrogen fumarate for use in preparing medicated drinking water for swine. See package insert for complete directions; read completely.

STORAGE AND HANDLING

Protect from direct sunlight. Store at controlled room temperature, 59 °–77 °F (15 °–25 °C).

Restricted Drug (California): Use only as directed

Description:

Denagard (tiamulin hydrogen fumarate) Liquid Concentrate is a solution containing 12.5 % tiamulin hydrogen fumarate (w/v) in an aqueous solution. The active ingredient, tiamulin hydrogen fumarate, chemically is 14-desoxy-14-[(2‑diethylaminoethyl) mercaptoacetoxy] mutilin hydrogen fumarate, a semi-synthetic diterpene antibiotic. Denagard Liquid Concentrate is for use only in preparing medicated drinking water for swine.

Actions: Tiamulin is active against Brachyspira (formerly Serpulina or Treponema) hyodysenteriae and Actinobacillus pleuropneumoniae. It is readily absorbed from the gut and can be found in the blood within 30 minutes after dosing.

Adverse Reactions:

Overdoses of Denagard have sometimes produced transitory salivation, vomiting and an apparent calming effect on the pig. If signs of toxicity occur, discontinue use of medicated water and replace with clean, fresh water.

In rare cases, redness of the skin primarily over the ham and underline has been observed during medication. If these signs appear, discontinue use of this drug. Provide ample clean drinking water. Thoroughly rinse (hose down) the housing to remove urine and feces from animal contact surfaces or move the animals to clean pens. If the condition persists, consult your veterinarian.

Studies to evaluate the safety of the water soluble form of tiamulin in breeding swine have not been done.

Use Directions:

The concentration of tiamulin hydrogen fumarate in the drinking water must be adjusted to compensate for variation in water consumption due to weight or size of the pig, environmental temperature and other factors. It is important that pigs receive the proper drug dose, 3.5 mg tiamulin hydrogen fumarate per pound for swine dysentery or 10.5 mg tiamulin hydrogen fumarate per pound for swine pneumonia, each day for 5 consecutive days.

Directions for preparing Denagard medicated solutions

Determine the amount of Denagard Liquid Concentrate needed to medicate the desired volume of drinking water at the proper concentration. Carefully measure out this amount, add it to the water and stir to thoroughly mix.

Number of pigs this bottle will treat for ONE day based on water consumption per pig |  | One Liter
Net tiamulin hydrogen fumarate content: |  | 125,000 mg
Diseases to be treated: |  | Swine Dysentery | Swine Pneumonia
Daily tiamulin hydrogen fumarate required per pound body weight: |  | 3.5 mg | 10.5 mg
Required treatment duration: |  | 5 days | 5 days
Pig Wt, lb | Water Intake, gal | # of Pigs | # of Pigs
20 | 0.3 - 0.5 | 1,786 | 595
45 | 0.4 - 1.1 | 794 | 265
75 | 0.7 - 1.5 | 476 | 159
125 | 1.0 - 2.0 | 286 | 95
180 | 1.2 - 3.0 | 198 | 66
Suggested final dilution of: | 1 bottle (1 Liter) | 550 gal | 183 gal
Suggested final dilution of: | 3 bottles (3 Liters) | 1650 gal | 550 gal
Suggested final dilution of: | ½ bottle (0.5 Liters) | 275 gal | 92 gal
Tiamulin hydrogen fumarate concentration per gallon at suggested final dilution* |  | 227 mg (60 ppm) | 681 mg (180 ppm)
1. Prepare fresh medicated drinking water every day for the 5 day treatment period.
2. Water medicated with Denagard should be the only source of drinking water during the treatment period.
*3. Increase or decrease dilution rate as required to obtain proper daily drug dose.

Number of pigs this bottle will treat for ONE day based on water consumption per pig |  | Five Liters
Net tiamulin hydrogen fumarate content: |  | 625,000 mg
Diseases to be treated: |  | Swine Dysentery | Swine Pneumonia
Daily tiamulin hydrogen fumarate required per pound body weight: |  | 3.5 mg | 10.5 mg
Required treatment duration: |  | 5 days | 5 days
Pig Wt, lb | Water Intake, gal | # of Pigs | # of Pigs
20 | 0.3 - 0.5 | 8,930 | 2,975
45 | 0.4 - 1.1 | 3,970 | 1,325
75 | 0.7 - 1.5 | 2,380 | 795
125 | 1.0 - 2.0 | 1,430 | 475
180 | 1.2 - 3.0 | 990 | 330
Suggested final dilution of: | 1 bottle (5 Liters) | 2750 gal | 917 gal
Suggested final dilution of: | 3 bottles (15 Liters) | 8250 gal | 2750 gal
Suggested final dilution of: | ½ bottle (2.5 Liters) | 1375 gal | 458 gal
Tiamulin hydrogen fumarate concentration per gallon at suggested final dilution* |  | 227 mg (60 ppm) | 681 mg (180 ppm)
1. Prepare fresh medicated drinking water every day for the 5 day treatment period.
2. Water medicated with Denagard should be the only source of drinking water during the treatment period.
*3. Increase or decrease dilution rate as required to obtain proper daily drug dose.

Directions for using Denagard

In medicated proportioners: One liter of Denagard Liquid Concentrate mixed with water to make 4.3 gallons of stock solution and this stock solution metered at one fluid ounce per gallon will provide 227 mg of tiamulin hydrogen fumarate per gallon to 550 gallons of drinking water for treatment of swine dysentery. Three liters of Denagard Liquid Concentrate mixed with water to make 4.3 gallons of stock solution and this stock solution metered at one fluid ounce per gallon will provide 681 mg tiamulin hydrogen fumarate per gallon to a total of 550 gallons of drinking water for treatment of swine pneumonia.

In medicated proportioners: Five liters of Denagard Liquid Concentrate mixed with water to make 21.5 gallons of stock solution and this stock solution metered at one fluid ounce per gallon will provide 227 mg of tiamulin hydrogen fumarate per gallon to 2750 gallons of drinking water for treatment of swine dysentery. Fifteen liters of Denagard Liquid Concentrate mixed with water to make 21.5 gallons of stock solution and this stock solution metered at one fluid ounce per gallon will provide 681 mg tiamulin hydrogen fumarate per gallon to a total of 2750 gallons of drinking water for treatment of swine pneumonia.

In barrels or tanks: One liter (1000 mL) of Denagard Liquid Concentrate will medicate 550 gallons of drinking water at 227 mg per gallon for treatment of swine dysentery or 183 gallons at 681 mg per gallon for treatment of swine pneumonia.

Measure Denagard Liquid Concentrate carefully, pour into the proper amount of water and thoroughly mix. The concentration of tiamulin hydrogen fumarate in the stock solution and in the drinking water delivered must be adjusted to compensate for variation in water consumption by pigs due to body weight, environmental and other factors. It is important that the pigs receive the proper drug dose of 3.5 mg of tiamulin hydrogen fumarate per pound of body weight daily for 5 consecutive days for treatment of swine dysentery or a dose of 10.5 mg per pound body weight daily for 5 consecutive days for treatment of swine pneumonia.

Attention: If no response to treatment is obtained within 5 days re-establish the diagnosis. Failure of response may be related to the presence of non-susceptible organisms of other complicating disease conditions. Because of the tendency for the disease to recur on premises with a history of swine dysentery or with swine pneumonia, a control program should be implemented after treatment. Drugs are not substitutes for proper sanitary measures or good management, but should be used in conjunction with such practices.

How supplied:

Container Size | Active Ingredients
1 Liter bottle (33.8 fl oz; 1000 mL) | 12.5% (125.0 g) | Tiamulin hydrogen fumarate
5 Liter bottle (169 fl oz; 5000 mL) | 12.5% (625.0 g) | Tiamulin hydrogen fumarate

Observe expiration date.

Questions/Comments? For technical assistance or to report side effects, contact Elanco US Inc. at 1-800-428-4441. For additional information about reporting side effects for animal drugs, contact FDA at 1-888-FDA-VETS or http://www.fda.gov/reportanimalae.

YL950193C 311545

Approved by FDA under NADA # 140-916

Denagard, Elanco and the diagonal bar logo are trademarks of Elanco or its affiliates.

© 2025 Elanco or its affiliates

Product 607728

Product of Italy
Manufactured for: Elanco US Inc.
Indianapolis, IN 46221

ElancoTM

Principal Display Panel - Denagard 1000 mL Bottle Label

Dengard™ 12.5%
(tiamulin hydrogen fumarate)

Liquid Concentrate

12.5% Tiamulin hydrogen fumarate
Approved by FDA under NADA # 140-916
One Liter (1.057 Quarts)
(33.8 fl oz; 1000 mL)

Principal Display Panel - Denagard 5000 mL Bottle Label

Dengard™ 12.5%
(tiamulin hydrogen fumarate)

5L Liquid
Concentrate

12.5% Tiamulin hydrogen fumarate
Approved by FDA under NADA # 140-916
Five Liter (5.285 Quarts)
(169 fl oz; 5000 mL)